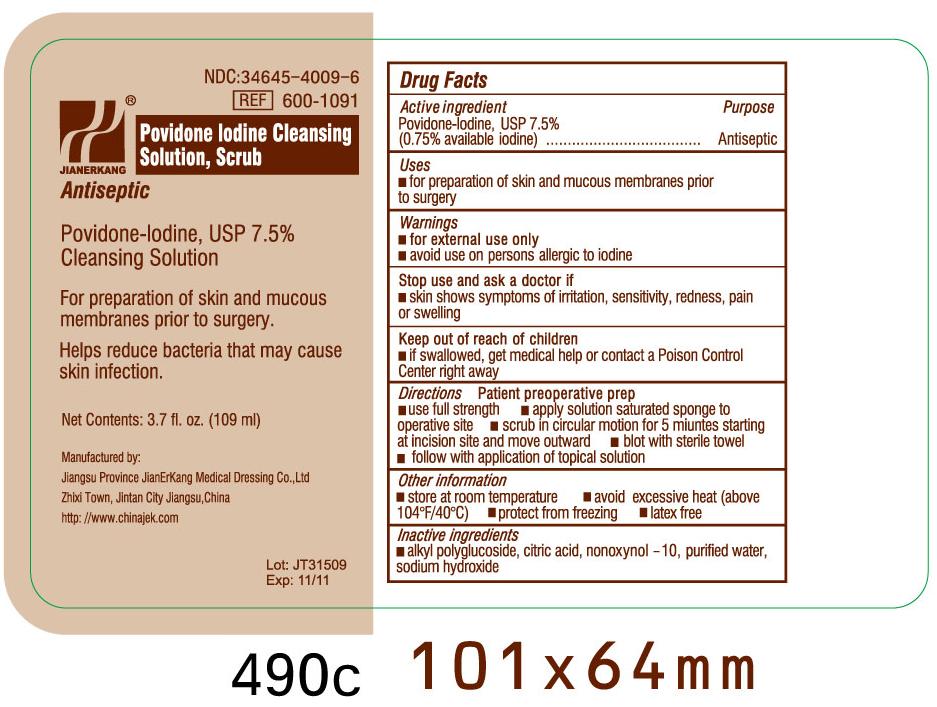 DRUG LABEL: Povidone Iodine
NDC: 34645-4009 | Form: SOLUTION
Manufacturer: Jianerkang Medical Co., Ltd
Category: otc | Type: HUMAN OTC DRUG LABEL
Date: 20231023

ACTIVE INGREDIENTS: POVIDONE-IODINE 7.5 mg/1 mL
INACTIVE INGREDIENTS: CITRIC ACID MONOHYDRATE; NONOXYNOL-10; WATER; SODIUM HYDROXIDE

Drug Facts

Active Ingredients

Povidone Iodine, USP 7.5% (0.75% available Iodine)

Purpose

Antiseptic

Uses

For preparation of skin and mucous membranes prior to surgery

Warnings

For external use only

Avoid use on persons allergic to iodine

Stop use and ask a doctor if

Skin shows symptoms of irritation, sensitivity, redness, pain or swelling

Keep out of reach of children

If swallowed, get medical help or contact Poison Control Center right away

Directions

Patient preoperative prep

use full strength

apply solution saturated sponge to operative site

scrub in circular motion for 5 minutes starting at incision site and move outward

blot with sterile towel

follow with application of topical solution

Other information

store at room temperature avoid excessive heat (above104oF/40oC) protect from freezing latex free

Inactive Ingredients

alkyl polyglucoside, citric acid, nonoxynol - 10, purified water, sodium hydroxide